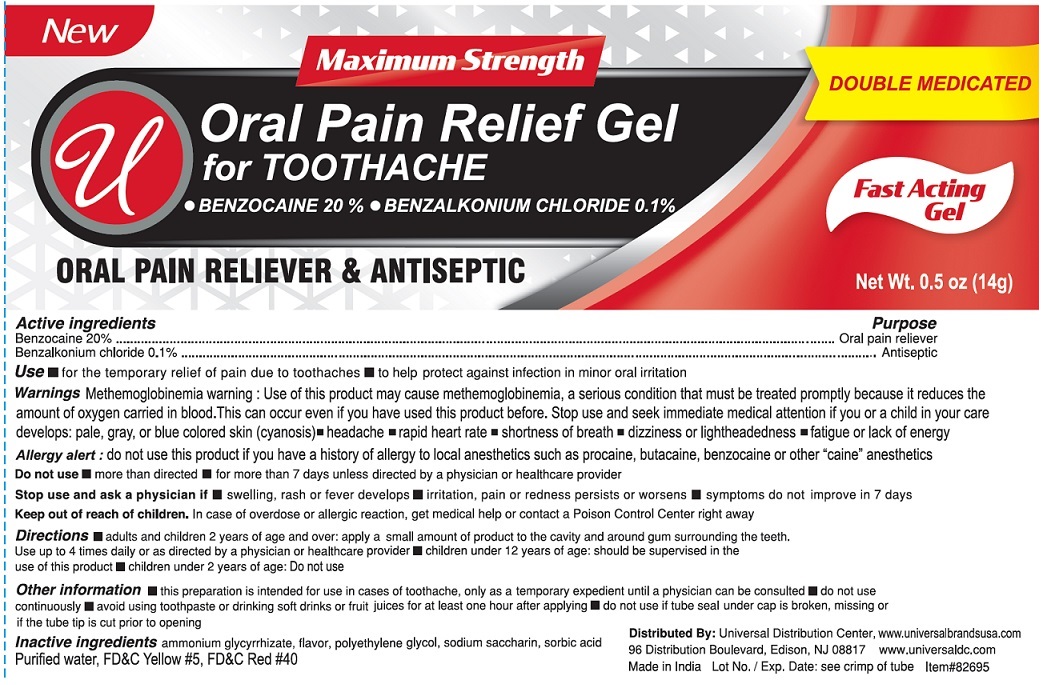 DRUG LABEL: Oral Pain Relief
NDC: 52000-060 | Form: GEL
Manufacturer: Universal Distribution Center LLC
Category: otc | Type: HUMAN OTC DRUG LABEL
Date: 20251030

ACTIVE INGREDIENTS: BENZOCAINE 0.2 g/1 g; BENZALKONIUM CHLORIDE 0.01 g/1 g
INACTIVE INGREDIENTS: AMMONIUM GLYCYRRHIZATE; POLYETHYLENE GLYCOL, UNSPECIFIED; SACCHARIN SODIUM; SORBIC ACID; WATER; FD&C YELLOW NO. 5; FD&C RED NO. 40

Oral Pain Relief Gel

Active Ingredients

Benzocaine 20%

Benzalkonium Chloride 0.1%

Purpose

Oral pain reliever

Antiseptic

Use

■ for the temporary relief of pain due to toothaches

■ to help protect against infection in minor oral irritation

Warnings

Methemoglobinemia warning: Use of this product may cause methemoglobinemia, a serious condition that must be treated promptly because it reduce the amount of oxygen carried in blood. This can occur even if you have used this product before. Stop use and seek immediate medical attention if you or a child in your care develops: pale, gray, or blue colored skin (cyanosis)
• headache
• rapid heart rate
• shortness of breath
• dizziness or lightheadness
• fatigue or lack of energy

Allergy alert:do not use this product if you have a history of allergy to local anesthetics such as procaine, butacaine or other "caine" anesthetics

Do not use

■ more than directed

■ for more than 7 days unless directed by a physician or healthcare provider

Stop use and ask a physician if

■ swelling, rash or fever develops

■ irritation, pain or redness persists or worsens

■ symptoms do not improve in 7 days

Keep out of reach of children

In case of overdose or allergic reaction get medical help or contact a Poison Control Center right away.

Directions

■ adults and children 2 years of age and over: apply a small amount of the product to the cavity and around the gum surrounding the teeth Use up to 4 times daily or as directed by a physician or healthcare provider

■ children under 12 years of age: should be supervised in the use of this product

■ children under 2 years of age: Do not use

Other information

■ this preparation is intended for use in cases ot toothache, only as a temporary expedient until a physican can be consulted

■ do not use continuously

■ avoid using toothpaste or drinking soft drinks or fruit juices for at least one hour after applying

■ do not use if tube seal under cap is broken, missing or if the tube tip is cut prior to opening

Inactive ingredients

ammonium glycyrrhizate, flavor, polyethylene glycol, sodium saccharin, sorbic acid, purified water, FD&C Yellow#5, FD&C Red#40

Package Label

Oral Pain Relief Gel

NET WT. 0.5 oz (14 g)